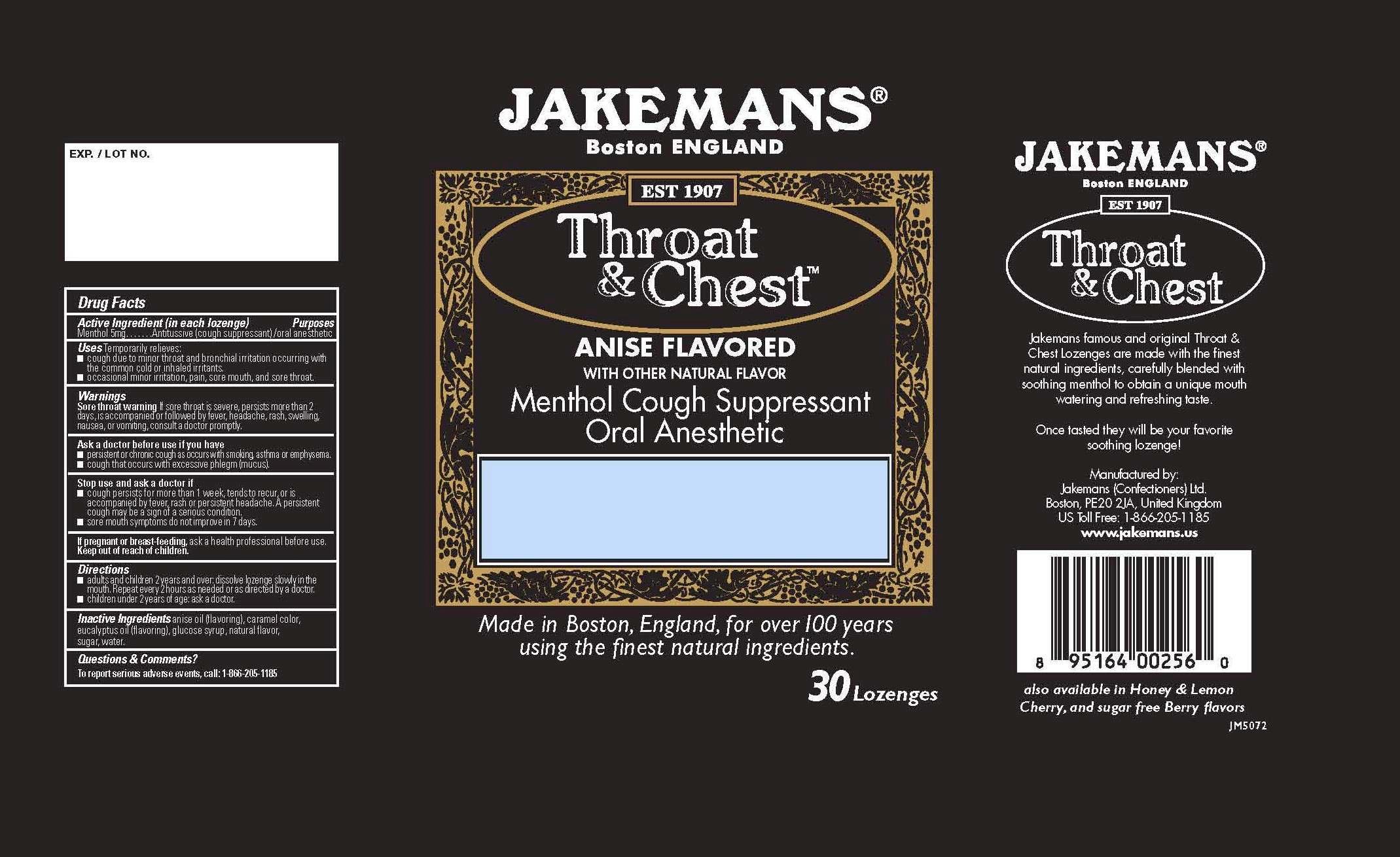 DRUG LABEL: Jakemans Throat and Chest Anise
NDC: 42637-827 | Form: LOZENGE
Manufacturer: Jakemans (Confectioners) Limited
Category: otc | Type: HUMAN OTC DRUG LABEL
Date: 20231023

ACTIVE INGREDIENTS: MENTHOL 5 mg/1 1
INACTIVE INGREDIENTS: ANISE OIL; EUCALYPTUS OIL; CARAMEL; MALIC ACID; SUCROSE; WATER

Jakemans Throat and Chest Anise

Drug Facts

Active Ingredient (in each lozenge)...Purpose
Menthol 5mg.........Antitussive (cough suppressant) / oral anesthetic

Menthol 5mg.........Antitussive (cough suppressant) / oral anesthetic

Uses

Temporarily relieves

cough due to minor throat and brochial irritation occurring with the common cold or inhaled irritants.
occasional minor irritation, pain, sore mouth, and sore throat.

Warnings
Sore throat warning.

If sore throat is severe, persists more than 2 days, is accompanied or followed by fever, headache, rash, swelling, nausea, or vomiting, consult a doctor promptly.

Ask a doctor before use if you have

- persistent or chronic cough as occurs with smoking, asthma or emphysema.
- cough that occurs with excessive phlegm (mucus).

Stop use and ask a doctor if

- cough persists for man than 1 week, tends to recur, or is accompanied by fever, rash or persistent headache. A persistent cough mat be a sign of a serious condition.
- sore mouth symptoms do not improve in 7 days.

If pregnant of breast-feeding,

ask a health professional before use.

Keep out of reach of children.

Inactive Ingredients

anise oil (flavoring), caramel color, eucalyptus oil (flavoring), glucose syrup, natural flavor, sugar, water.

Questions and Comments?

To report serious adverse enets, call: 1-866-205-1185

Directions

- adults and children 2 years and over dissolve lozenge slowly in the mouth. Repear every 2 hours as needed or as directed by a doctor.
- children under 2 years of age ask a doctor.

PACKAGE LABEL

JAKEMANS
Boston ENGLAND
EST 1907
Throat and Chest
Anise Flavored
With other Natural Flavor
Menthol Cough Suppressant
Oral Anesthetic

Made in Boston, England, for over 100 years
using the finest natural ingredients
24 LOZENGES